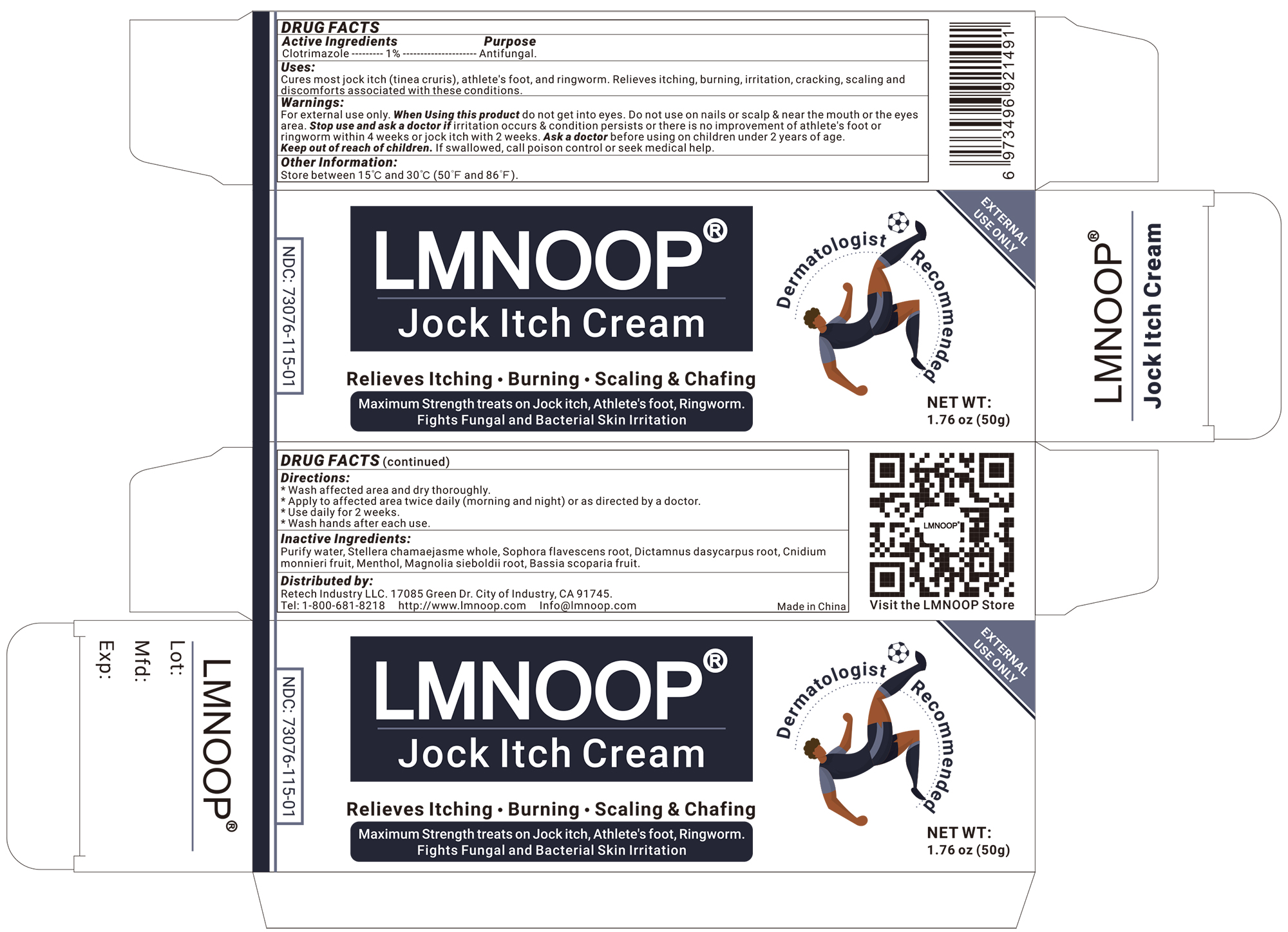 DRUG LABEL: LMNOOP Jock Itch Cream
NDC: 73076-206 | Form: CREAM
Manufacturer: Shenzhen Ishan Technology Co., Ltd
Category: homeopathic | Type: HUMAN OTC DRUG LABEL
Date: 20260213

ACTIVE INGREDIENTS: OATMEAL 1 g/100 g
INACTIVE INGREDIENTS: WATER; SOPHORA FLAVESCENS ROOT 3 g/100 g; DICTAMNUS DASYCARPUS ROOT 3 g/100 g; BASSIA SCOPARIA FRUIT 3 g/100 g; MAGNOLIA SIEBOLDII ROOT 3 g/100 g; CNIDIUM MONNIERI FRUIT 3 g/100 g; STELLERA CHAMAEJASME WHOLE 3 g/100 g; MENTHOL 1 g/100 g

Active Ingredients

Clotrimazole----1%----Antifungal

Inactive Ingredients

Purify water, dictamnus dasycarpus root, stellera chamaejasme whole, sophora flavescens root, cnidium monnieri fruit, phellodendron chinense whole, Menthol. Magnolia Sieboldii Root

Keep out of reach of children.

if swallowed, call poison control or seek medical help.

Stop use and ask a doctor if

Irritation occurs & condition persists or there is no improvement of athlete's foot or ringworm within 4 weeks or jock intch with 2 weeks.

Stop use if

Irritation occurs & condition persists or there is no improvement of athlete's foot or ringworm within 4 weeks or jock itch with 2 weeks

USES:

Cures most ringworm, athlete's foot and jock itch.
Relieves itching, burning, irritation and discomforts which may accompany these conditions

Other information

Store between 15℃ and 30℃ (50℉ and 86℉)

Directions:

* Wash affected area and dry thoroughly
* Apply a thin layer iShanCare over affected area twice daily (morning and night) or as directed by a doctor.
* For athlete's foot, pay special attention to spaces between toes; wear well fitting, ventilated shoes, change shoes and socks at least once daily.
* For athlete's foot and ringworm, use daily for 4 weeks.
* For jock itch, use daily for 2 weeks.
* For fungal infection on toe use brush applicator to apply under nail and around cuticle. This product is not proven to be effective on scalp or nails.

When Using this product

do not get into eyes. do not apply to wounds or damaged skin.

Warning:

For external use only.